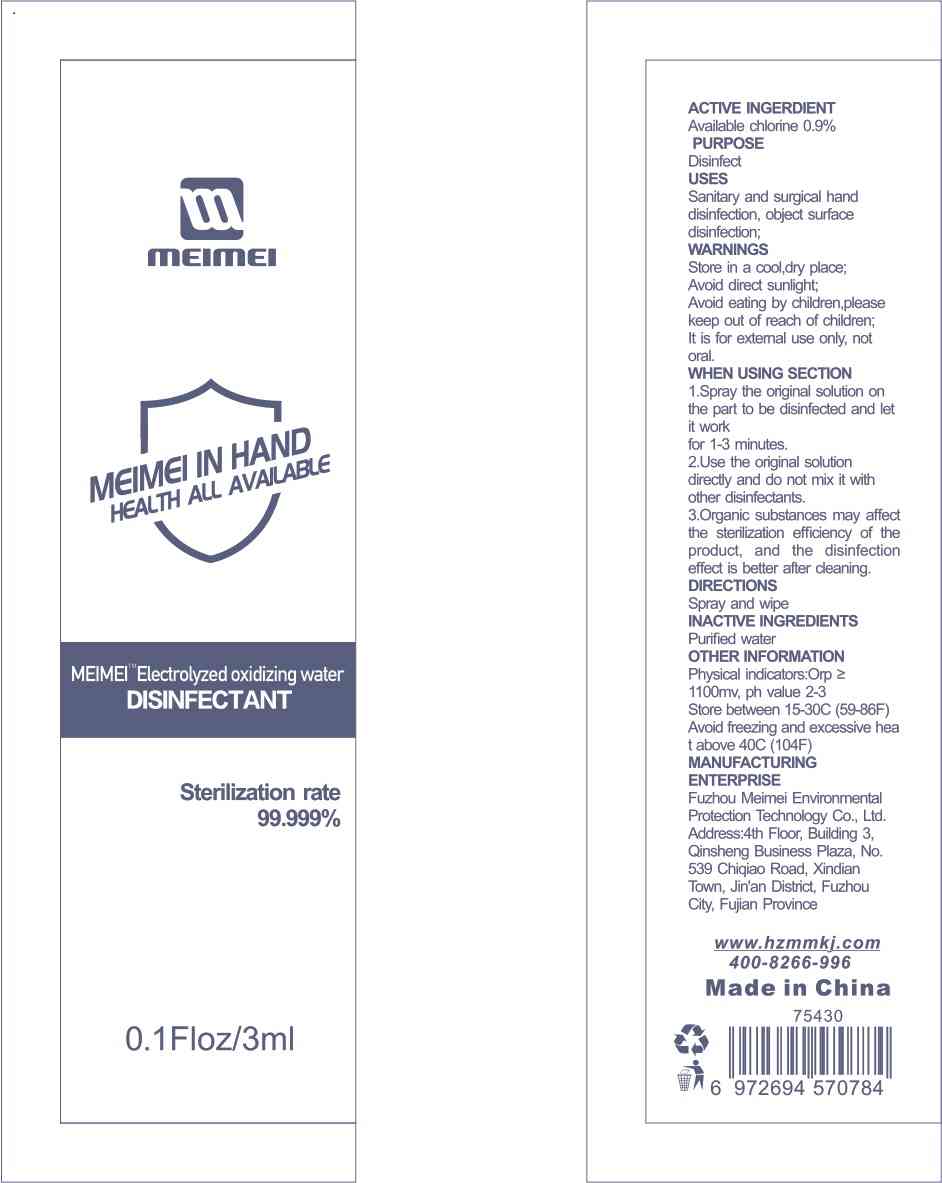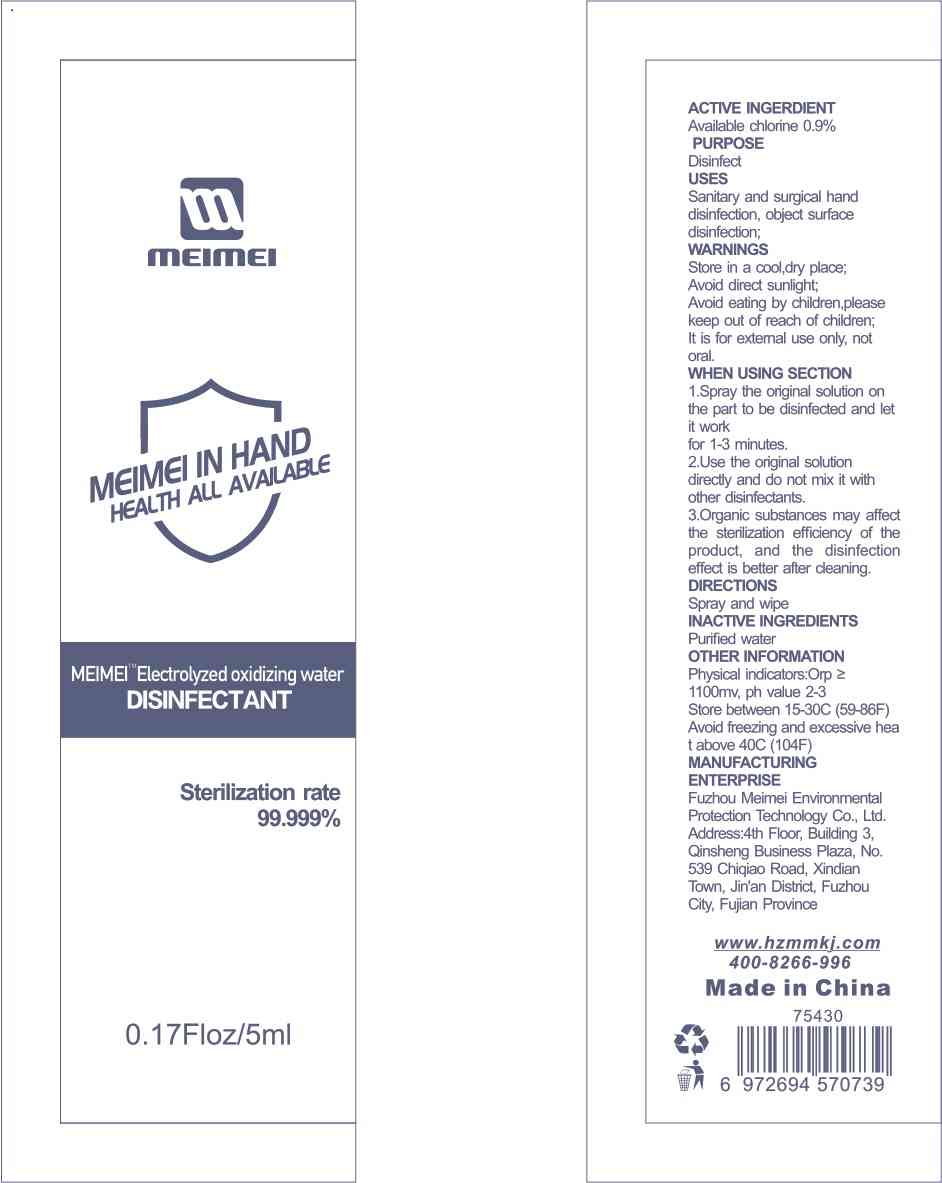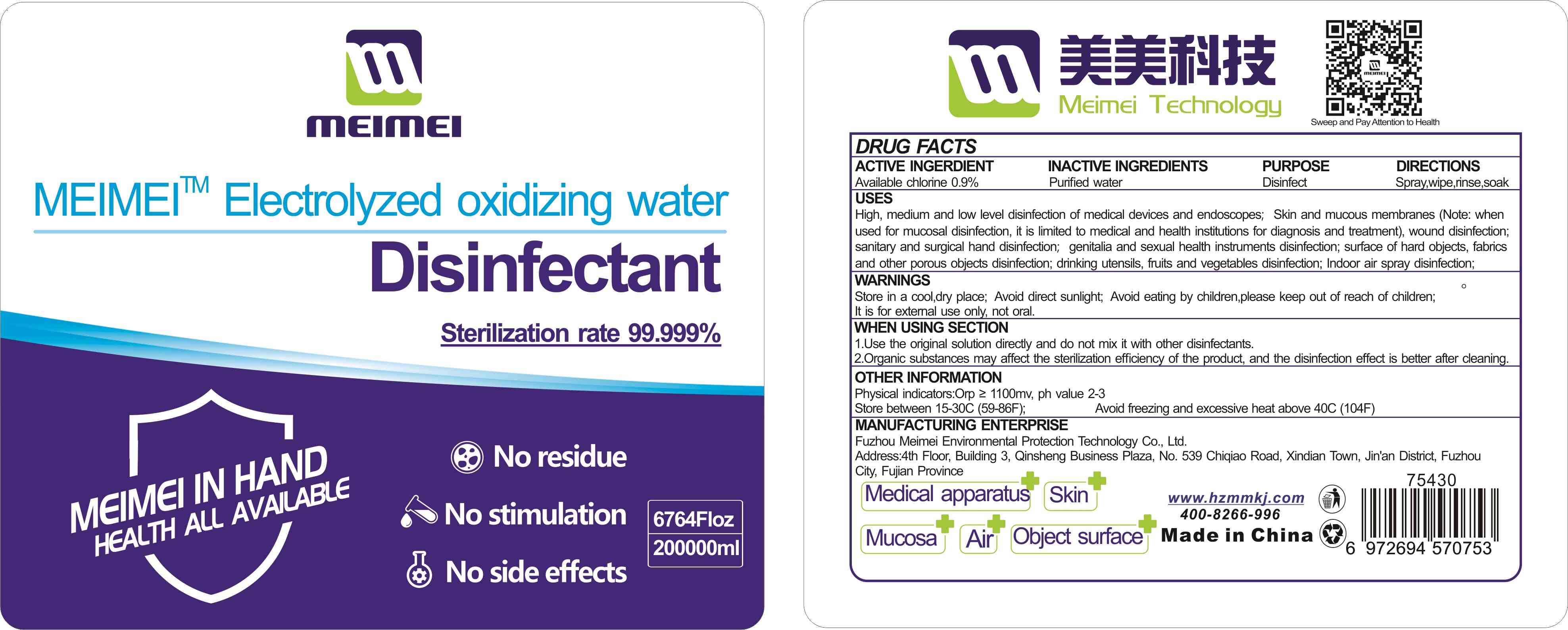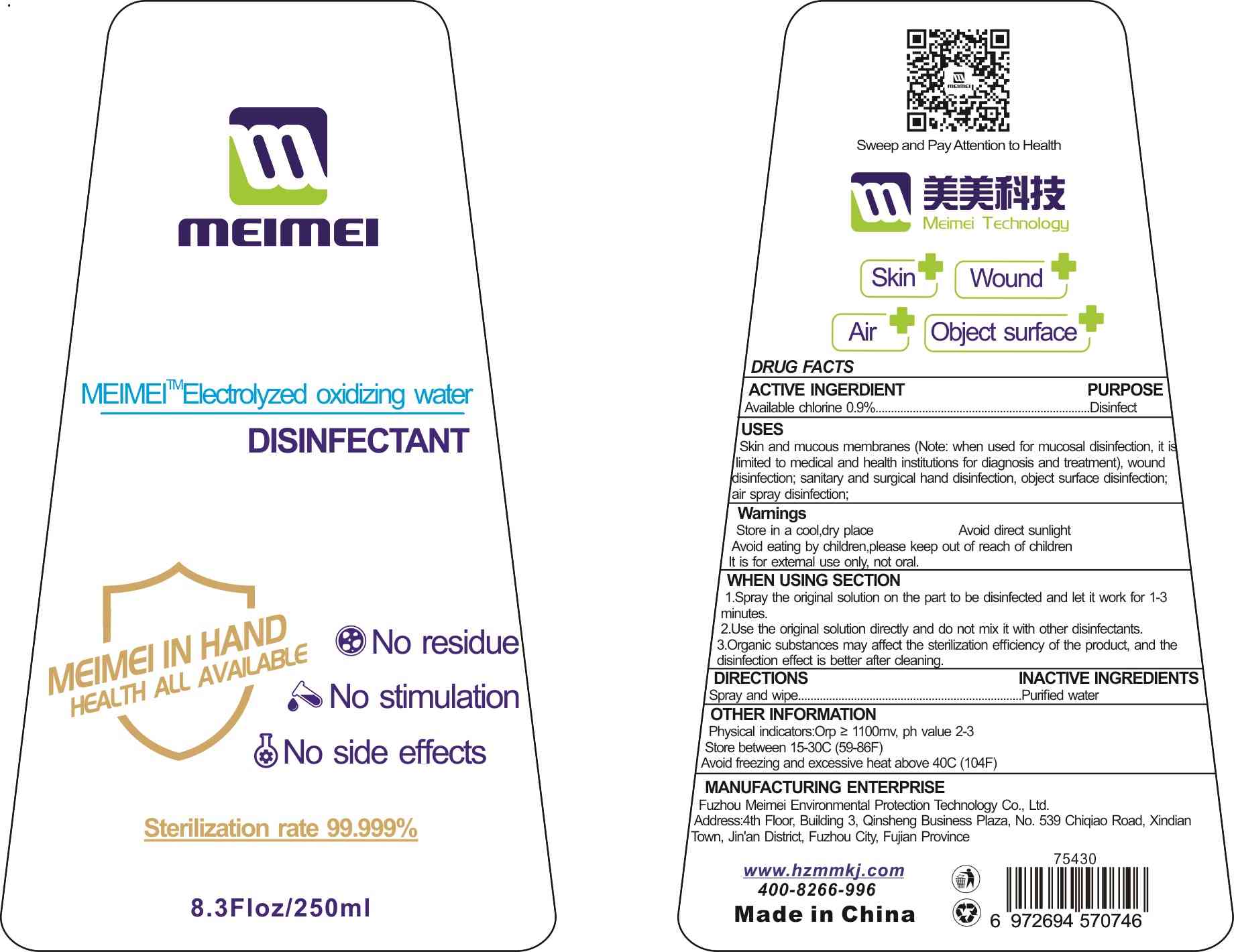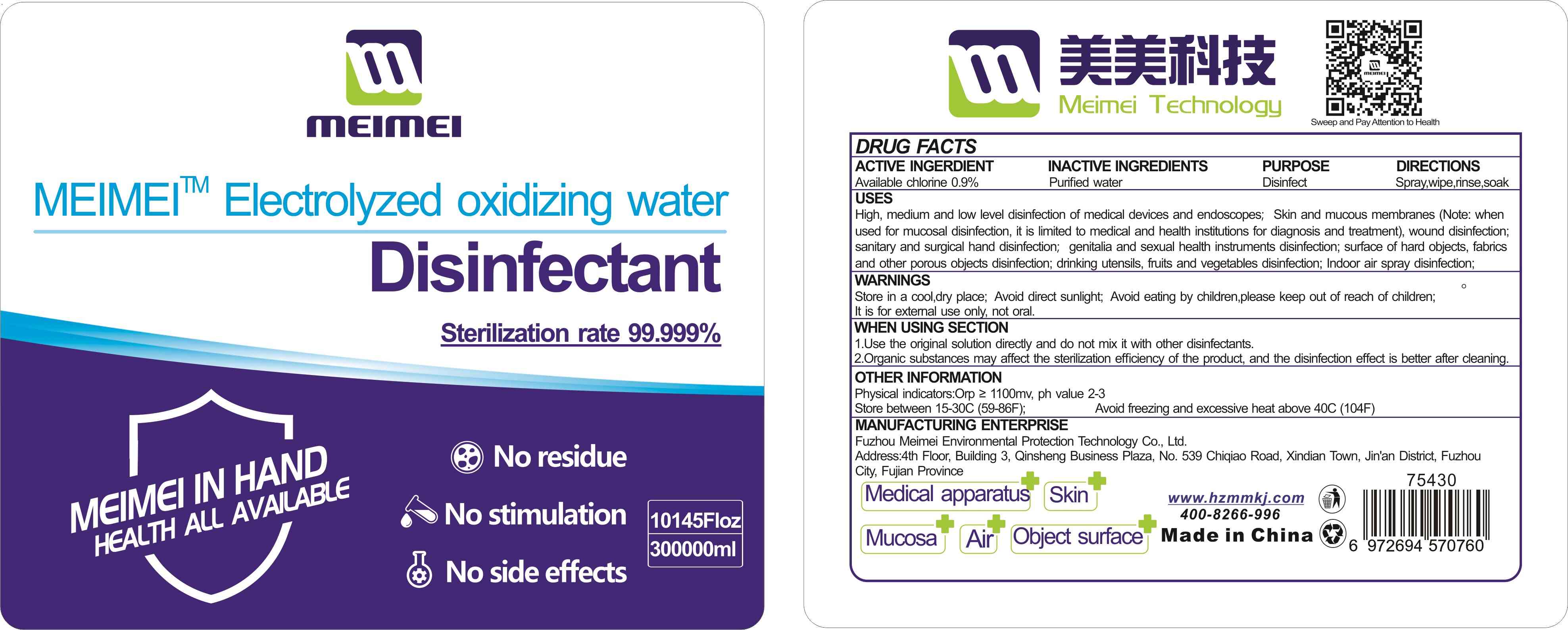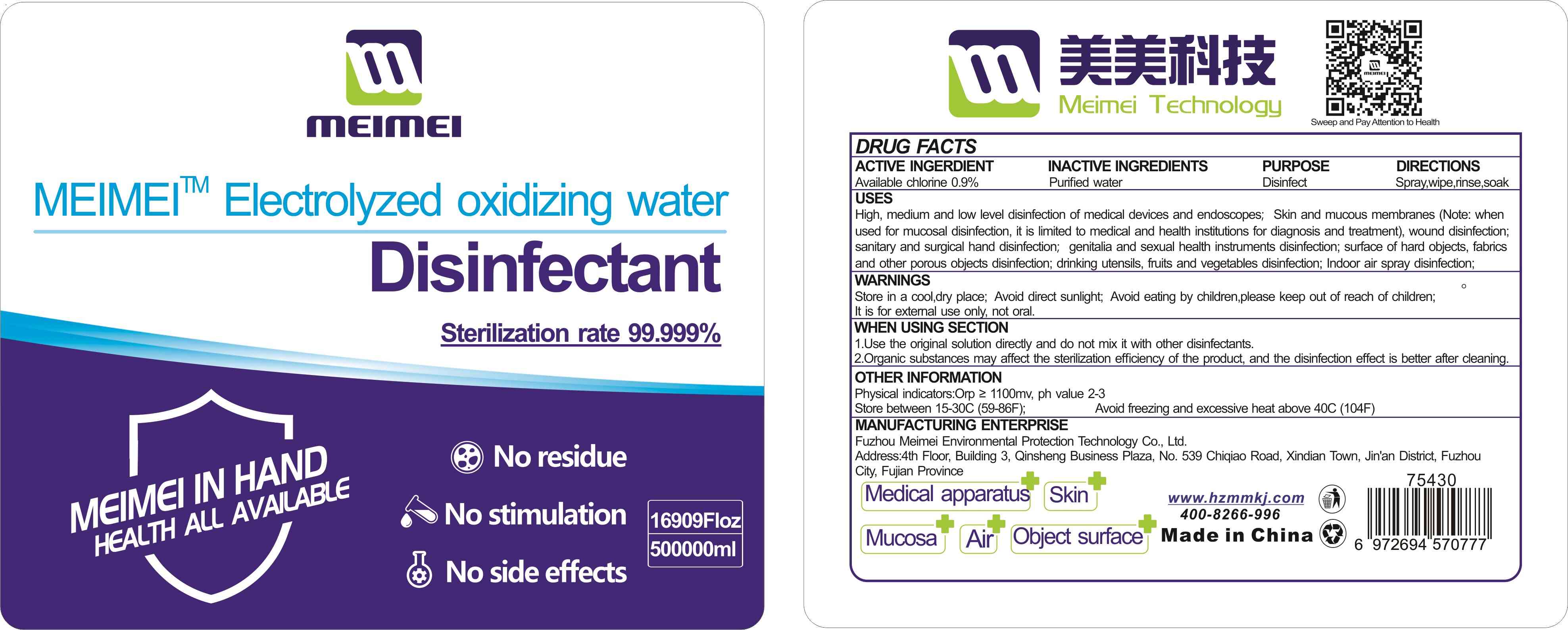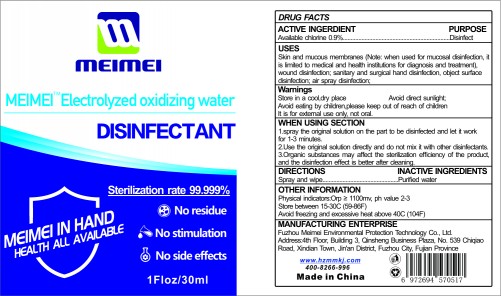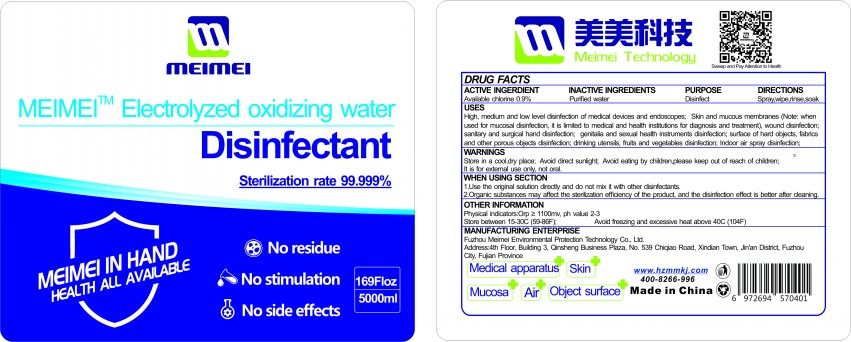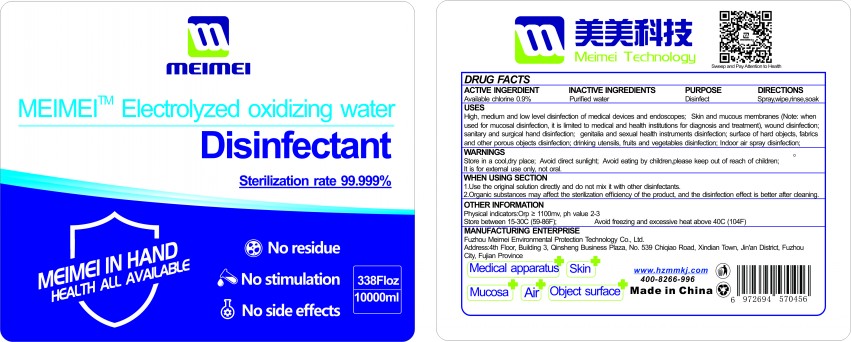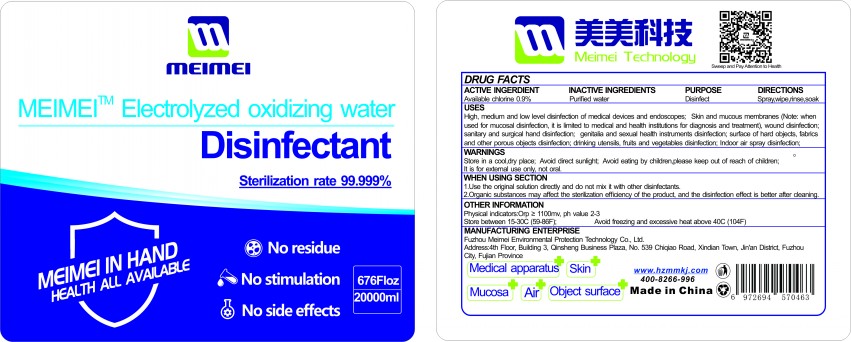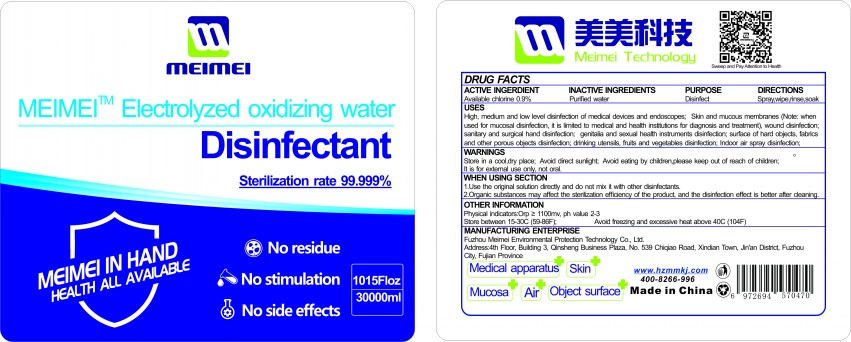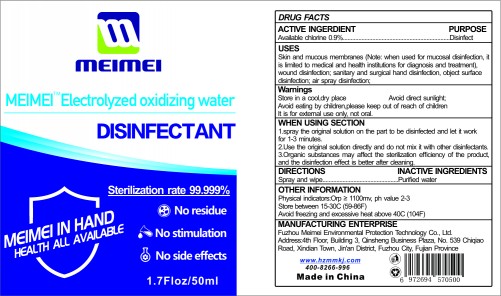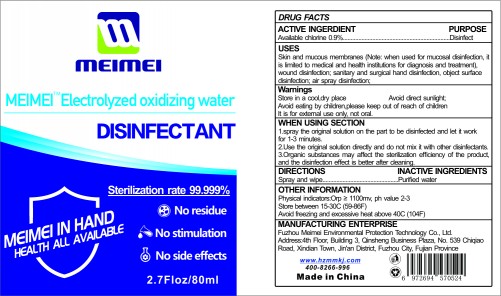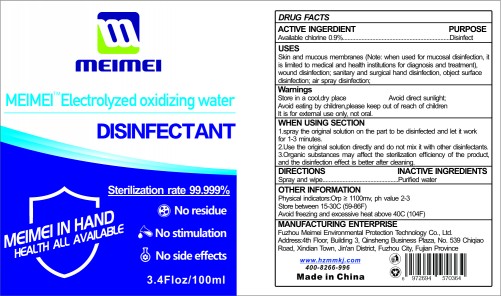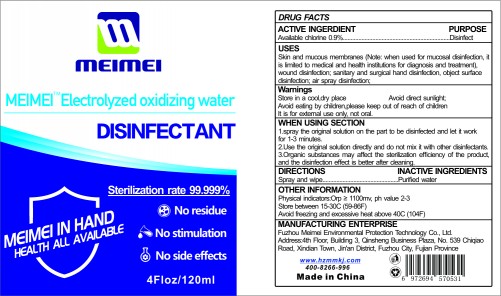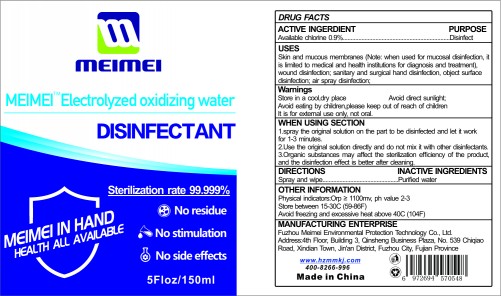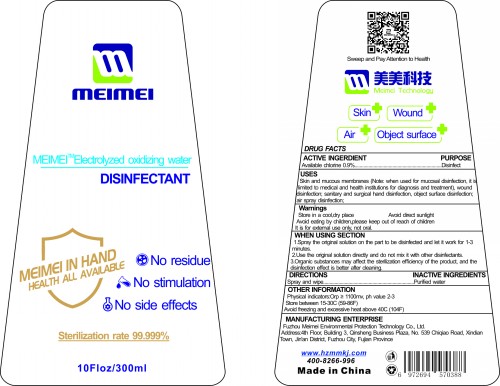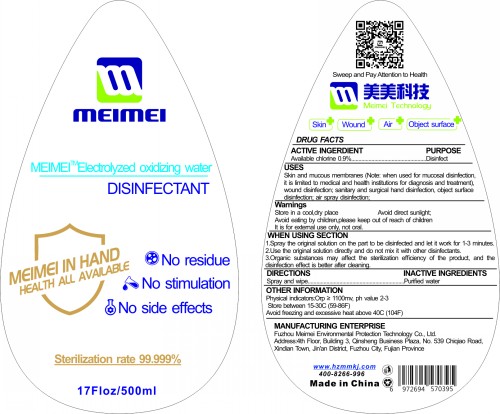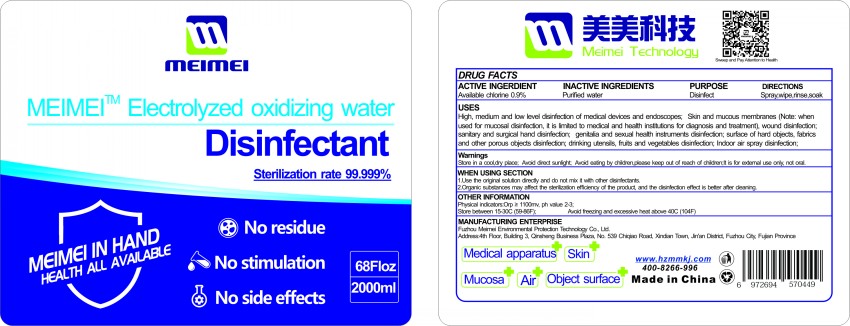 DRUG LABEL: Electrolyzed-oxidizing Water Disinfectant
NDC: 75430-001 | Form: SPRAY
Manufacturer: Fuzhou Meimei Environmental Protection Technology Co., Ltd.
Category: otc | Type: HUMAN OTC DRUG LABEL
Date: 20220328

ACTIVE INGREDIENTS: HYPOCHLOROUS ACID 0.9 g/100 mL
INACTIVE INGREDIENTS: WATER

Electrolyzed-oxidizing Water Disinfectant

ACTIVE INGERDIENT

Available chlorine 0.9%

PURPOSE

Disinfect

USES

High,medium and low level disinfection of medical devices and endoscopes;Skin and mucous membranes (Note:when

used for mucosal disinfection,it is limited to medical and health institutions for diagnosis and treatment),wound disinfection;

sanitary and surgical hand disinfection; genitalia and sexual health instruments disinfection;surface of hard objects,fabrics

and other porous objects disinfection;drinking utensils, fruits and vegetables disinfection;Indoor air spray disinfection;

Warnings

Store in a cool,dry place; Avoid direct sunlight; Avoid eating by children, please keep out of reach of children; It is for external use only,not oral.

WHEN USING SECTION

1.Use the original solution directly and do not mix it with other disinfectants.

2.Organic substances may affect the sterilization efficiency of the product,and the disinfection effect is better after cleaning.

DIRECTIONS

Spray,wipe,rinse, soak

OTHER INFORMATION

Physical indicators:Orp≥1100mv,ph value 2-3;

Store between 15-30C(59-86F) ; Avoid freezing and excessive heat above 40C(104F)

INACTIVE INGREDIENTS

Purified water